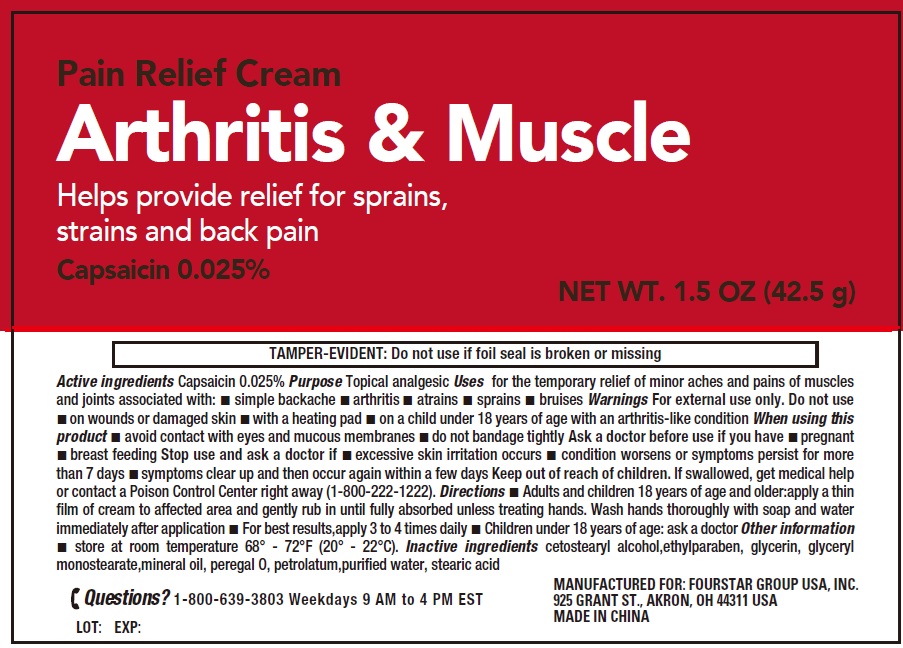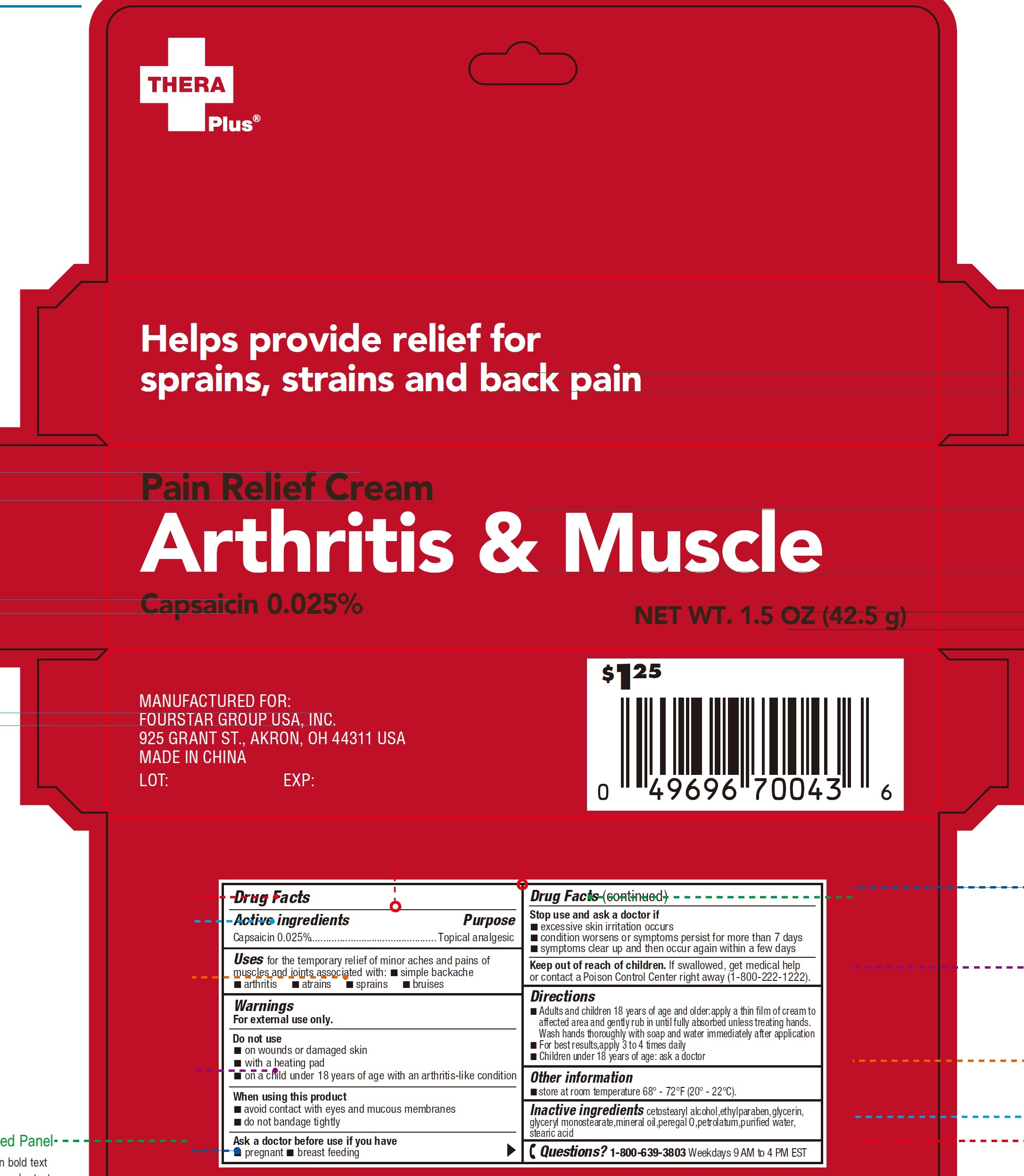 DRUG LABEL: Thera Plus Pain Relief Arthritis and Muscle
NDC: 80684-138 | Form: CREAM
Manufacturer: FOURSTAR GROUP USA, INC.
Category: otc | Type: HUMAN OTC DRUG LABEL
Date: 20250228

ACTIVE INGREDIENTS: CAPSAICIN 0.25 mg/1 g
INACTIVE INGREDIENTS: CETOSTEARYL ALCOHOL; ETHYLPARABEN; GLYCERIN; GLYCERYL MONOSTEARATE; MINERAL OIL; PETROLATUM; WATER; STEARIC ACID

Thera Plus Pain Relief Cream Arthritis and Muscle

Active ingredients

Capsaicin 0.025%

Purpose

Topical analgesic

Uses

for the temporary relief of minor aches and pains of muscles and joints associated with:

- simple backache
- arthritis
- atrains
- sprains
- bruises

Warnings

For external use only.

Do not use

- on wounds or damaged skin
- with a heating pad
- on a child under 18 years of age with an arthritis-like condition

When using this product

- avoid contact with eyes and mucous membranes
- do not bandage tightly

Ask a doctor before use if you have

- pregnant
- breast feeding

Stop use and ask a doctor if

- excessive skin irritation occurs
- condition worsens or symptoms persist for more than 7 days
- symptoms clear up and then occur again within a few days

Keep out of reach of children.

If swallowed, get medical help or contact a Poison Control Center right away (1-800-222-1222).

Directions

- Adults and children 18 years of age and older:apply a thin film of cream to affected area and gently rub in until fully absorbed unless treating hands. Wash hands thoroughly with soap and water immediately after application
- For best results,apply 3 to 4 times daily
- Children under 18 years of age: ask a doctor

Other information

- store at room temperature 68° - 72°F (20° - 22°C).

Inactive ingredients

cetostearyl alcohol,ethylparaben,glycerin,glyceryl monostearate,mineral oil,peregal O,petrolatum,purified water,stearic acid

Questions?

1-800-639-3803Weekdays 9 AM to 4 PM EST